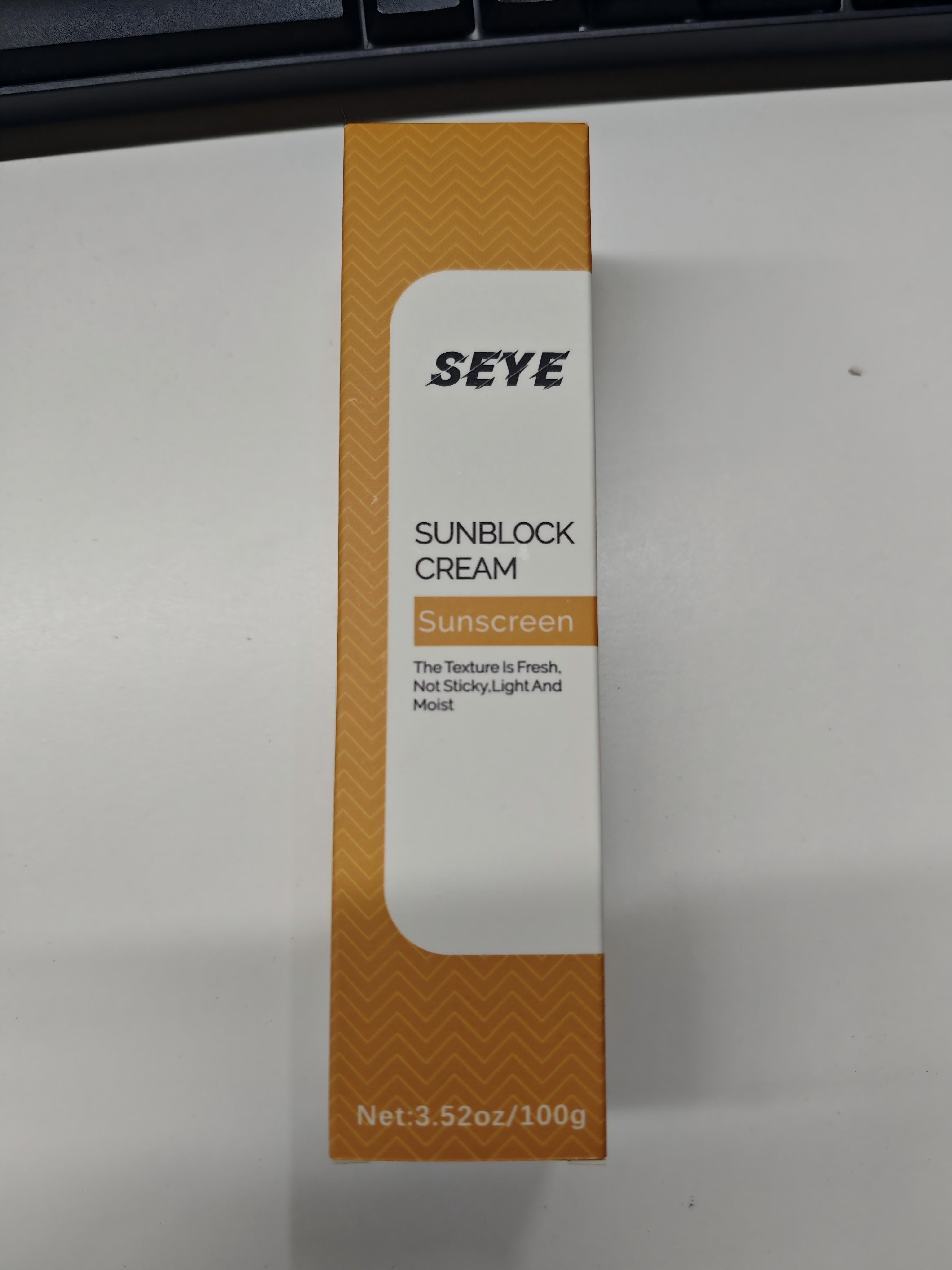 DRUG LABEL: SEYE
NDC: 87044-1201 | Form: CREAM
Manufacturer: Guangzhou Seye Biomedical Technology Co., Ltd.
Category: otc | Type: HUMAN OTC DRUG LABEL
Date: 20250820

ACTIVE INGREDIENTS: TITANIUM DIOXIDE 10 g/100 g; ZINC OXIDE 20 g/100 g
INACTIVE INGREDIENTS: ETHYLHEXYL PALMITATE 4 g/100 g; ALOE BARBADENSIS LEAF JUICE 0.001 g/100 g; ISOHEXADECANE 1.602 g/100 g; 1,2-HEXANEDIOL 0.5 g/100 g; SQUALANE 3 g/100 g; OLEA EUROPAEA (OLIVE) FRUIT OIL 0.001 g/100 g; AQUA 52.991 g/100 g; GLYCERIN 5 g/100 g; CYCLODEXTRIN 0.0009 g/100 g; ALPHA-TOCOPHEROL ACETATE 0.001 g/100 g; CARBOMER 0.2 g/100 g; BUTYLENE GLYCOL 0.001 g/100 g; CENTELLA ASIATICA LEAF 0.001 g/100 g; HYDROXYACETOPHENONE 0.5 g/100 g; C12-20 ALKYL GLUCOSIDE 0.26 g/100 g; XANTHAN GUM 0.2 g/100 g; C14-22 ALCOHOLS 1.04 g/100 g; POTASSIUM CETYL PHOSPHATE 0.5 g/100 g; ARGININE 0.2 g/100 g; PAEONIA LACTIFLORA ROOT 0.001 g/100 g; CERAMIDE NP 0.0001 g/100 g

Active ingredient(s)

- Zinc Oxide 20%
- Titanium Dioxide 10%

Purpose(s)

- Sunscreen
- Sunscreen

Uses

- Helps prevent sunburn
- If used as directed with other sun protection measures (see Directions), decreases the risk of skin cancer and early skin aging caused by the sun

Warnings

For external use only.

Do not use

- On damaged or broken skin

When using this product

- Keep out of eyes. Rinse with water to remove

Stop use and ask a doctor if

- Rash occurs

Pregnancy or breast feeding section

If pregnant or breast-feeding, ask a health professional before use.

Keep out of reach of children

If swallowed, get medical help or contact a Poison Control Center right away.

Directions

- Apply liberally 15 minutes before sun exposure
- Reapply at least every 2 hours
- Use a water-resistant sunscreen if swimming or sweating
- Sun Protection Measures. Spending time in the sun increases your risk of skin cancer and early skin aging. To decrease this risk, regularly use a sunscreen with a Broad Spectrum SPF value of 15 or higher and other sun protection measures including:

1. limit time in the sun, especially from 10 a.m. - 2 p.m.

2. Wear long-sleeved shirts, pants, hats, and sunglasses

- Children under 6 months of age: Ask a doctor

Other information

- Protect this product from excessive heat and direct sun

Inactive ingredients

AQUA, ZINC OXIDE, TITANIUM DIOXIDE, GLYCERIN, ETHYLHEXYL PALMITATE, SQUALANE, ISOHEXADECANE, C14-22 ALCOHOLS, 1,2-HEXANEDIOL, POTASSIUM CETYL PHOSPHATE, HYDROXYACETOPHENONE, C12-20 ALKYL GLUCOSIDE, CARBOMER, ARGININE, XANTHAN GUM, BUTYLENE GLYCOL, ALPHA-TOCOPHEROL ACETATE, ALOE BARBADENSIS LEAF JUICE, CENTELLA ASIATICA LEAF, OLEA EUROPAEA (OLIVE) FRUIT OIL, PAEONIA LACTIFLORA ROOT, CERAMIDE NP, CYCLODEXTRIN

Questions or comments?

934-935-7135 / Yiqinzhi726@gmail.com

PACKAGE LABEL

The Texture Is Fresh, Not Sticky, Light And Moist.
Effectively blocks ultraviolet rays, prevents sunburn, photoaging, and pigmentation, while also having auxiliary functions such as moisturizing and skin conditioning to help maintain the skin's hydrated state during sun protection. Suitable for daily or outdoor protection needs.